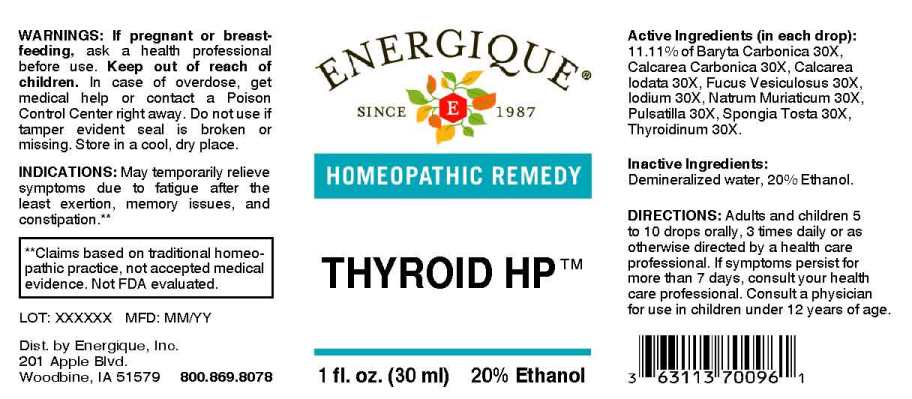 DRUG LABEL: Thyroid HP
NDC: 44911-0057 | Form: LIQUID
Manufacturer: Energique, Inc.
Category: homeopathic | Type: HUMAN OTC DRUG LABEL
Date: 20240911

ACTIVE INGREDIENTS: BARIUM CARBONATE 30 [hp_X]/1 mL; OYSTER SHELL CALCIUM CARBONATE, CRUDE 30 [hp_X]/1 mL; CALCIUM IODIDE 30 [hp_X]/1 mL; FUCUS VESICULOSUS 30 [hp_X]/1 mL; IODINE 30 [hp_X]/1 mL; SODIUM CHLORIDE 30 [hp_X]/1 mL; PULSATILLA VULGARIS WHOLE 30 [hp_X]/1 mL; SPONGIA OFFICINALIS SKELETON, ROASTED 30 [hp_X]/1 mL; THYROID 30 [hp_X]/1 mL
INACTIVE INGREDIENTS: WATER; ALCOHOL

Drug Facts:

ACTIVE INGREDIENTS:

(in each drop): 11.11% of Baryta Carbonica 30X, Calcarea Carbonica 30X, Calcarea Iodata 30X, Fucus Vesiculosus 30X, Iodium 30X, Natrum Muriaticum 30X, Pulsatilla (Vulgaris) 30X, Spongia Tosta 30X, Thyroidinum (Suis) 30X.

INDICATIONS:

May temporarily relieve symptoms due to fatigue after the least exertion, memory issues, and constipation.**

**Claims based on traditional homeopathic practice, not accepted medical evidence. Not FDA evaluated.

WARNINGS:

If pregnant or breast-feeding, ask a health professional before use.

Keep out of reach of children. In case of overdose, get medical help or contact a Poison Control Center right away.

Do not use if tamper evident seal is broken or missing. Store in a cool, dry place.

DIRECTIONS:

Adults and children 5 to 10 drops orally, 3 times daily or as otherwise directed by a health care professional. If symptoms persist for more than 7 days, consult your health care professional. Consult a physician for use in children under 12 years of age.

INACTIVE INGREDIENTS:

Demineralized water, 20% Ethanol.

Keep out of reach of children. In case of overdose, get medical help or contact a Poison Control Center right away.

INDICATIONS:

May temporarily relieve symptoms due to fatigue after the least exertion, memory issues and constipation.**

**Claims based on traditional homeopathic practice, not accepted medical evidence. Not FDA evaluated.

QUESTIONS:

Dist. by Energique, Inc.

201 Apple Blvd

Woodbine, IA 51579 800.869.8078

PACKAGE LABEL

ENERGIQUE

SINCE 1987

HOMEOPATHIC REMEDY

THYROID HP
1 fl. oz. (30 ml)